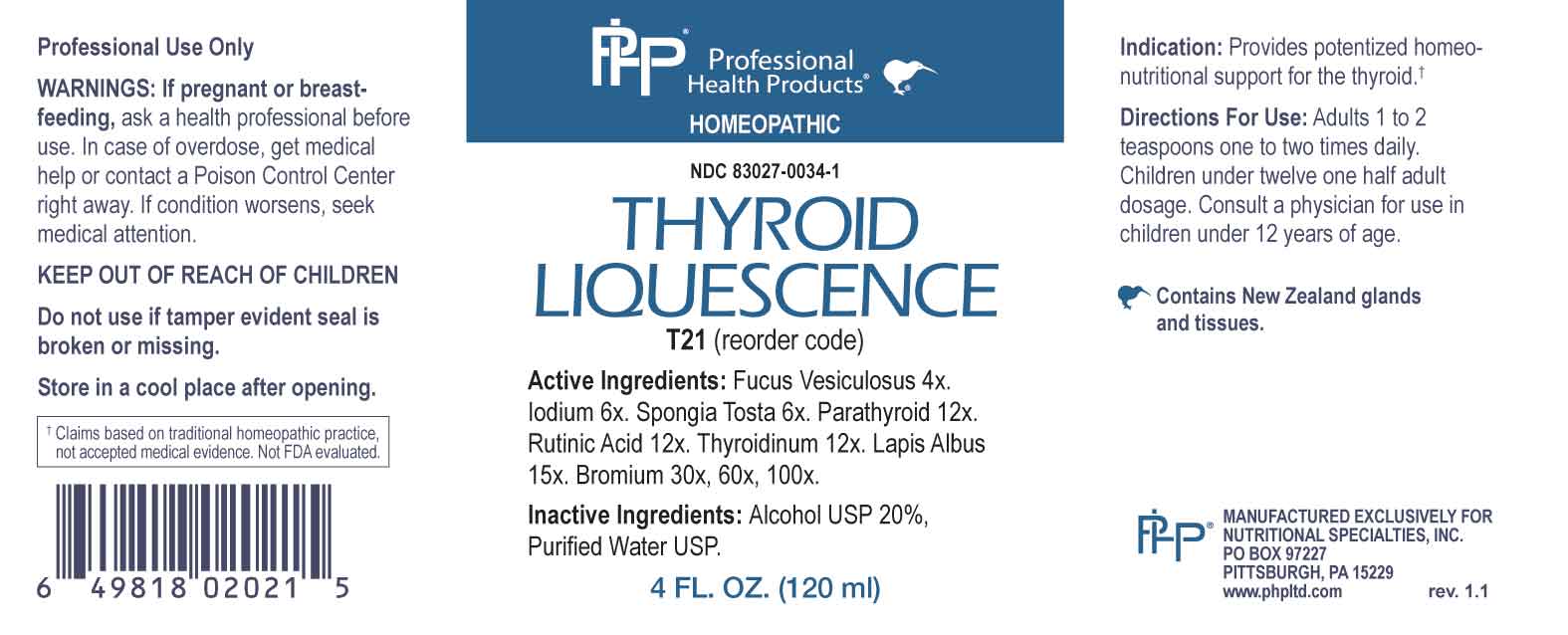 DRUG LABEL: Thyroid Liquescence
NDC: 83027-0034 | Form: LIQUID
Manufacturer: Nutritional Specialties, Inc.
Category: homeopathic | Type: HUMAN OTC DRUG LABEL
Date: 20240308

ACTIVE INGREDIENTS: FUCUS VESICULOSUS 4 [hp_X]/1 mL; IODINE 6 [hp_X]/1 mL; SPONGIA OFFICINALIS SKELETON, ROASTED 6 [hp_X]/1 mL; BOS TAURUS PARATHYROID GLAND 12 [hp_X]/1 mL; CAPRIC ACID 12 [hp_X]/1 mL; THYROID, BOVINE 12 [hp_X]/1 mL; CALCIUM HEXAFLUOROSILICATE 15 [hp_X]/1 mL; BROMINE 30 [hp_X]/1 mL
INACTIVE INGREDIENTS: WATER; ALCOHOL

DRUG FACTS:

ACTIVE INGREDIENTS:

Fucus Vesiculosus 4X, Iodium 6X, Spongia Tosta 6X, Parathyroid 12X, Rutinic Acid 12X, Thyroidinum 12X, Lapis Albus 15X, Bromium 30X, 60X, 100X.

PURPOSE:

Provides potentized homeo-nutritional support for the thyroid.†

†Claims based on traditional homeopathic practice, not accepted medical evidence. Not FDA evaluated.

WARNINGS:

Professional Use Only

If pregnant or breast-feeding, ask a health professional before use.

In case of overdose, get medical help or contact a Poison Control Center right away.

If condition worsens, seek medical attention.

KEEP OUT OF REACH OF CHILDREN

Do not use if tamper evident seal is broken or missing.

Store in a cool place after opening

KEEP OUT OF REACH OF CHILDREN:

In case of overdose, get medical help or contact a Poison Control Center right away.

DIRECTIONS:

Adults 1 to 2 teaspoons one to two times daily. Children under twelve one half adult dosage. Consult a physician for use in children under 12 years of age.

INDICATIONS:

Provides potentized homeo-nutritional support for the thyroid.†

†Claims based on traditional homeopathic practice, not accepted medical evidence. Not FDA evaluated.

INACTIVE INGREDIENTS:

Alcohol USP 20%, Purified Water USP.

QUESTIONS:

MANUFACTURED EXCLUSIVELY FOR

NUTRITIONAL SPECIALTIES, INC.

PO BOX 97227

PITTSBURG, PA 15229

www.phpltd.com

PACKAGE LABEL DISPLAY:

Professional

Health Products

HOMEOPATHIC

NDC 83027-0034-1

THYROID

LIQUESCENCE

4 FL. OZ (120 ml)